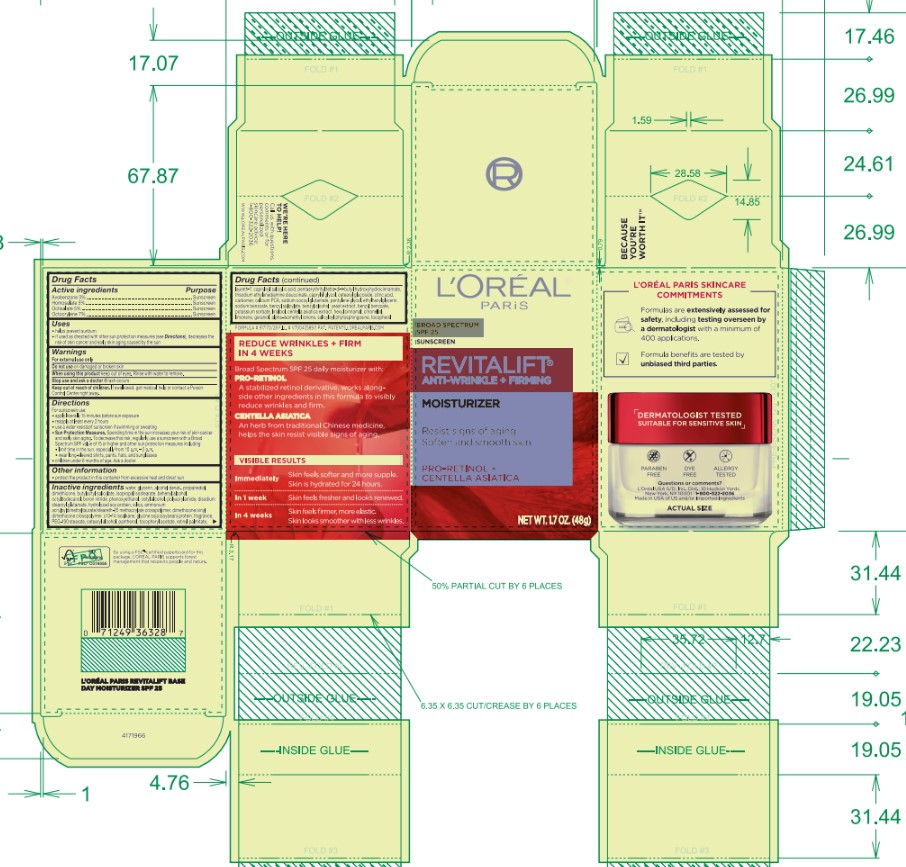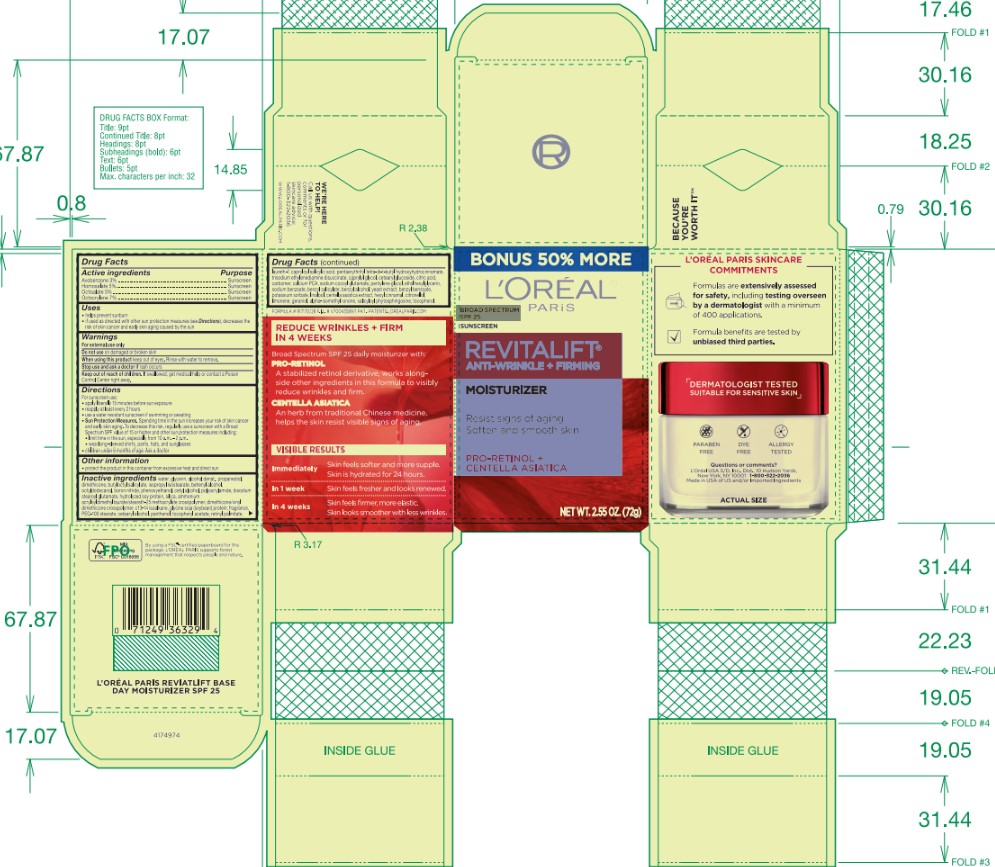 DRUG LABEL: LOreal Paris REVITALIFT Anti-Wrinkle plus Firming Broad Spectrum SPF 25 Moisturizer Sunscreen
NDC: 49967-329 | Form: CREAM
Manufacturer: L'Oreal USA Products Inc
Category: prescription | Type: HUMAN PRESCRIPTION DRUG LABEL
Date: 20260107

ACTIVE INGREDIENTS: Avobenzone 30 mg/1 mL; Homosalate 50 mg/1 mL; Octisalate 50 mg/1 mL; Octocrylene 70 mg/1 mL
INACTIVE INGREDIENTS: WATER; GLYCERIN; ALCOHOL; PROPANEDIOL; DIMETHICONE; BUTYLOCTYL SALICYLATE; ISOPROPYL ISOSTEARATE; DOCOSANOL; OCTYLDODECANOL; BORON NITRIDE; PHENOXYETHANOL; CETYL ALCOHOL; DISODIUM STEAROYL GLUTAMATE; HYDROLYZED SOY PROTEIN (ENZYMATIC; 2000 MW); SILICON DIOXIDE; C13-14 ISOPARAFFIN; SOY PROTEIN; PEG-100 STEARATE; CETOSTEARYL ALCOHOL; PANTHENOL; .ALPHA.-TOCOPHEROL ACETATE; VITAMIN A PALMITATE; LAURETH-7; CAPRYLOYL SALICYLIC ACID; PENTAERYTHRITOL TETRAKIS(3-(3,5-DI-TERT-BUTYL-4-HYDROXYPHENYL)PROPIONATE); TRISODIUM ETHYLENEDIAMINE DISUCCINATE; CAPRYLYL GLYCOL; CETEARYL GLUCOSIDE; CITRIC ACID MONOHYDRATE; CARBOMER HOMOPOLYMER, UNSPECIFIED TYPE; CALCIUM PIDOLATE; SODIUM COCOYL GLUTAMATE; PENTYLENE GLYCOL; ETHYLHEXYLGLYCERIN; SODIUM BENZOATE; BENZYL SALICYLATE; BENZYL ALCOHOL; YEAST, UNSPECIFIED; BENZYL BENZOATE; POTASSIUM SORBATE; LINALOOL, (+/-)-; CENTELLA ASIATICA TRITERPENOIDS; .ALPHA.-HEXYLCINNAMALDEHYDE; .BETA.-CITRONELLOL, (R)-; LIMONENE, (+)-; GERANIOL; ISOMETHYL-.ALPHA.-IONONE; SALICYLOYL PHYTOSPHINGOSINE; TOCOPHEROL

Drug Facts

Active ingredients

Avobenzone 3%

Homosalate 5%

Octisalate 5%

Octocrylene 7%

Purpose

Sunscreen

Uses

- helps prevent sunburn
- if used as directed with other sun protection measures (see Directions), decreases the risk of skin cancer and early skin aging caused by the sun

Warnings

For external use only

Do not use

on damaged or broken skin

When using this product

keep out of eyes. Rinse with water to remove.

Stop use and ask a doctor if

rash occurs

Keep out of reach of children.

If swallowed, get medical help or contact a Poison Control Center right away.

Directions

For sunscreen use:

- apply liberally 15 minutes before sun exposure
- reapply at least every 2 hours
- use a water resistant sunscren if swimming or sweating
- Sun Protection Measures. Spending time in the sun increases your risk of skin cancer and early skin aging. To decrease this risk, regularly use a sunscreen with a Broad Spectrum SPF value of 15 or higher and other sun protection measures including:
- limit time in the sun, especially from 10 a.m. - 2 p.m.
- wear long-sleeved shirts, pants, hats, and sunglasses
- children under 6 months of age: Ask a doctor

Other information

- protect the product in this container from excessive heat and direct sun

Inactive ingredients

water, glycerin, alcohol denat., propanediol, dimethicone, butyloctyl salicylate, isopropyl isostearate, behenyl alcohol, octyldodecanol, boron nitride, phenoxyethanol, cetyl alcohol, polyacrylamide, disodium stearoyl glutamate, hydrolyzed soy protein, silica, ammonium acryloyldimethyltaurate/steareth-25 methacrylate crosspolymer, dimethicone/vinyl dimethicone crosspolymer, c13-14 isoalkane, glycine soja (soybean) protein, fragrance, PEG-100 stearate, cetearyl alcohol, panthenol, tocopheryl acetate, retinyl palmitate, laureth-7, capryloyl salicylic acid, pentaerythrityl tetra-di-t-butyl hydroxyhydrocinnamate, trisodium ethylenediamine disuccinate, caprylyl glycol, cetearyl glucoside, citric acid, carbomer, calcium PCA, sodium cocoyl glutamate, pentylene glycol, ethylhexylglycerin, sodium benzoate, benzyl salicylate, benzyl alcohol, yeast extract, benzyl benzoate, potassium sorbate, linalool, centella asiatica extract, hexyl cinnamal, citronellol, limonene, geraniol, alpha-isomethyl ionone, salicyloyl phytosphingosine, tocopherol

Questions or comments?

L'Oreal USA S/D, Inc., Dist., 10 Hudson Yards,

New York, NY 10001 1-800-322-2036